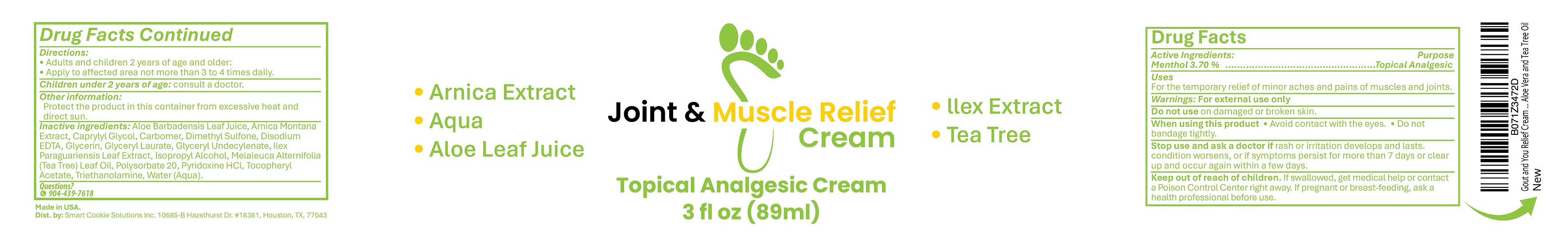 DRUG LABEL: Joint and Muscle Relief
NDC: 87282-001 | Form: CREAM
Manufacturer: Smart Cookie Solutions Inc.
Category: otc | Type: HUMAN OTC DRUG LABEL
Date: 20251212

ACTIVE INGREDIENTS: MENTHOL 37 mg/1 mL
INACTIVE INGREDIENTS: CARBOMER; POLYSORBATE 20; ALPHA-TOCOPHEROL ACETATE; ILEX PARAGUARIENSIS LEAF; DIMETHYL SULFONE; EDETATE DISODIUM; GLYCERIN; ISOPROPYL ALCOHOL; WATER; CAPRYLYL GLYCOL; MELALEUCA ALTERNIFOLIA (TEA TREE) LEAF OIL; ALOE BARBADENSIS LEAF JUICE; GLYCERYL LAURATE; PYRIDOXINE HCL; TRIETHANOLAMINE; ARNICA MONTANA; GLYCERYL 1-UNDECYLENATE

Joint & Muscle Relief Cream

Active ingredient:

Menthol 3.70%

Purpose

Topical Analgesic

Uses

For the temporary relief of minor aches and pains of muscles and joints.

Warnings: For external use only

Do not use on damaged or broken skin.

When using this product • Avoid contact with the eyes. • Do not bandage tightly.

Stop use and ask a doctor if rash or irritation develops and lasts, condition worsens, or if symptoms persist for more than 7 days or clear up and occur again within a few days.

Keep out of reach of children. If swallowed, get medical help or contacct a Poison Control Center right away.

PREGNANCY OR BREAST FEEDING

If pregnant or breast-feeding, ask a health professional before use.

Directions:

- Adults and children 2 years of age and older:
- Apply to affected area not more than 3 to 4 times daily.
- Children under 2 years of age: consult a doctor.

Other information

Protect the product in this container from excessive heat and direct sun.

INACTIVE INGREDIENT

Inactive ingredients: aloe barbadensis leaf juice, arnica montana extract, caprylyl glycol, carbomer, dimethyl sulfone, disodium EDTA, glycerin, glyceryl laurate, glyceryl undecylenate, ilex paraguariensis leaf extract, isopropyl alcohol, melaleuca alternifolia (tea tree) leaf oil, polysorbate 20, pyridoxine HCl, tocopheryl acetate, triethanolamine, water(aqua).

Questions?

904-439-7618

Made in USA

Dist. by: Smart Cookie Solutions Inc. 10685-B Hazelhurst Dr. #18381, Houston, TX 77043

PACKAGE LABEL

Joint & Muscle Relief

Cream

Topical Analgesic Cream

• Arnica Extract • Ilex Extract

• Aqua • Tea Tree

• Aloe Leaf Juice

3 fl oz (89ml)